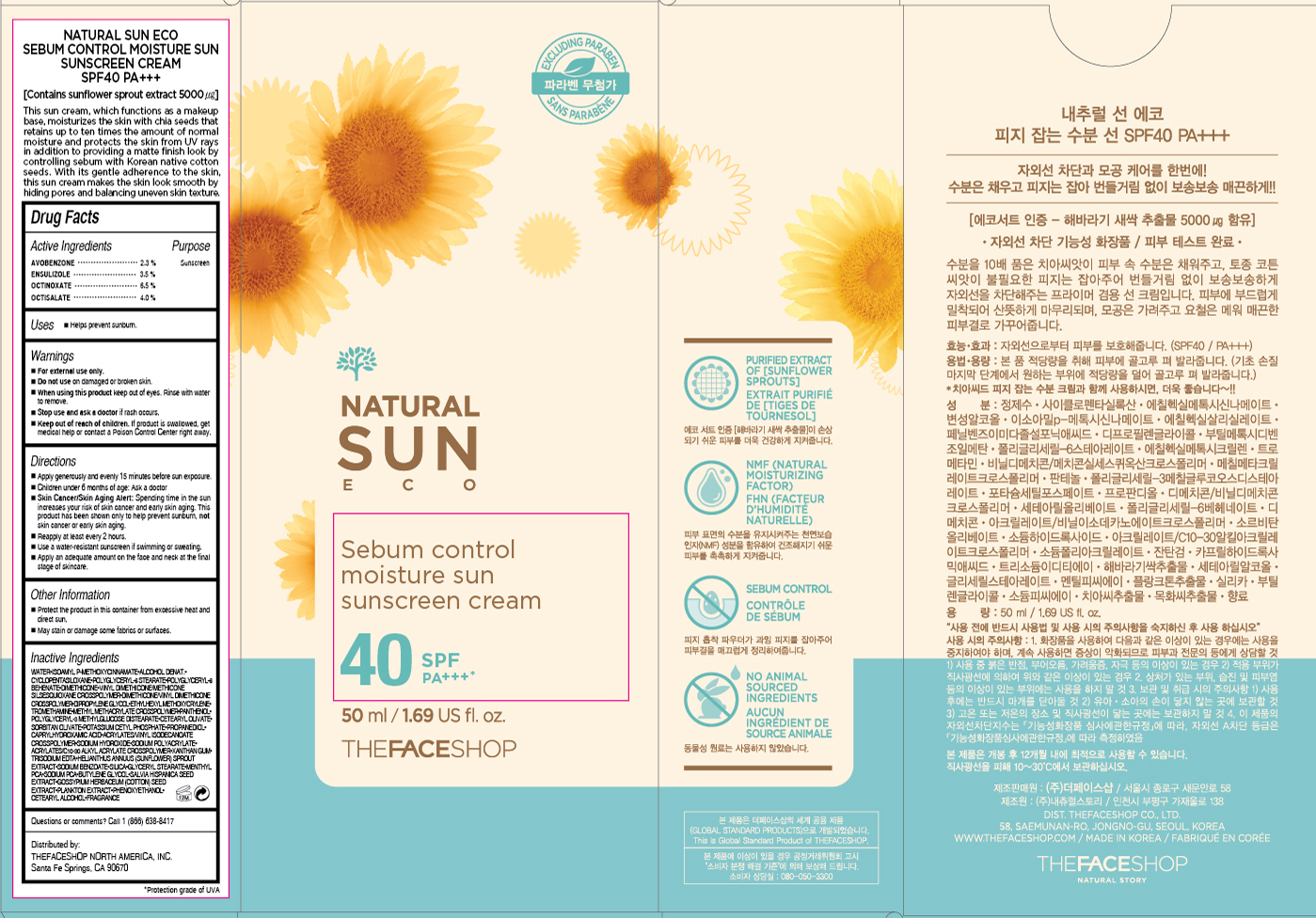 DRUG LABEL: NATURAL SUN ECO
NDC: 51523-168 | Form: CREAM
Manufacturer: THEFACESHOP CO., LTD.
Category: otc | Type: HUMAN OTC DRUG LABEL
Date: 20151201

ACTIVE INGREDIENTS: AVOBENZONE 1.2 g/50 mL; OCTISALATE 2 g/50 mL; ENSULIZOLE 1.8 g/50 mL; OCTINOXATE 3.3 g/50 mL
INACTIVE INGREDIENTS: WATER

NATURAL SUN ECO SUNSCREEN CREAM 40 SPF PA+++ 31500168

Active Ingredients

Avobenzone 2.3 %

Ensulizole 3.5%

Octinoxate 6.5 %

Octisalate 4.0%

Purpose

Sunscreen

Sunscreen

Sunscreen

Warnings

For external use only.

Do not use on damaged or broken skin

When using this product keep out of eyes. Rinse with water to remove.

Stop use and ask a doctor if rash occurs.

Keep out of reach of children. If product is swallowed, get medical help or contact a Poison Control Center right away.

Directions

Apply generously and evenly 15 minutes before sun exposure.
Children under 6 months of age: Ask a doctor.
Skin Cancer/Skin Aging Alert: Spending time in the sun increases your risk of skin cancer and early skin aging.

This product has been shown only to help prevent sunburn, not skin cancer or early skin aging.
Reapply at least every 2 hours.
Use a water-resistant sunscreen if swimming or sweating.

Apply an adequate amount on the face and neck at the final stage of skincare.

Other Information

Protect the product in this container from excessive heat and direct sun.

May stain or damage some fabrics or surfaces.

Inactive Ingredients

WATER, ISOAMYL P-METHOXYCINNAMATE,ALCOHOL DENAT.,CYCLOPENTASILOXANE,POLYGLYCERYL-6 STEARATE,POLYGLYCERYL-6 BEHENATE,DIMETHICONE,VINYL DIMETHICONE/METHICONE SILSESQUIOXANE CROSSPOLYMER,DIMETHICONE/VINYL DIMETHICONE CROSSPOLYMER,DIPROPYLENE GLYCOL,ETHYLHEXYL METHOXYCRYLENE,TROMETHAMINE,METHYL METHACRYLATE CROSSPOLYMER,PANTHENOL,POLYGLYCERYL-3 METHYLGLUCOSE DISTEARATE, CETEARYL OLIVATE, SORBITAN OLIVATE, POTASSIUM CETYL PHOSPHATE, PROPANEDIOL, CAPRYLHYDROXAMIC ACID, ACRYLATES/VINYL ISODECANOATE CROSSPOLYMER, SODIUM HYDROXIDE, SODIUM , POLYACRYLATE, ACRYLATES/C10-30 ALKYL ACRYLATE CROSSPOLYMER, XANTHAN GUM, TRISODIUM EDTA, HELIANTHUS ANNUUS (SUNFLOWER) SPROUT EXTRACT, SODIUM BENZOATE, SILICA, GLYCERYL STEARATE, MENTHYL PCA, SODIUM PCA, BUTYLENE GLYCOL, SALVIA HISPANICA SEED EXTRACT, GOSSYPIUM HERBACEUM (COTTON) SEED EXTRACT, PLANKTON EXTRACT, PHENOXYETHANOL, CETEARYL ALCOHOL, FRAGRANCE

Questions or comments?

Call 1-866-638-8417

Distributed by:

THEFACESHOP NORTH AMERICA, INC.

Santa Fe Springs, CA 90670

Label

NATURAL SUN ECO SUNSCREEN CREAM

SEBUM CONTROL MOISTURE SUN

SPF40 PA+++

[Contains sunflower sprout extract 5000 µg]

This sun cream, which functions as a makeup base,

moisturizes the skin with chia seeds that retains up

to ten times the amount of normal moisture and protects

the skin from UV rays in addition to providing a matte finish

look by controlling sebum with Korean native cotton seeds.

With its gentle adherence to the skin, the sun cream makes

the skin look smooth by hiding pores and balancing uneven

skin texture.